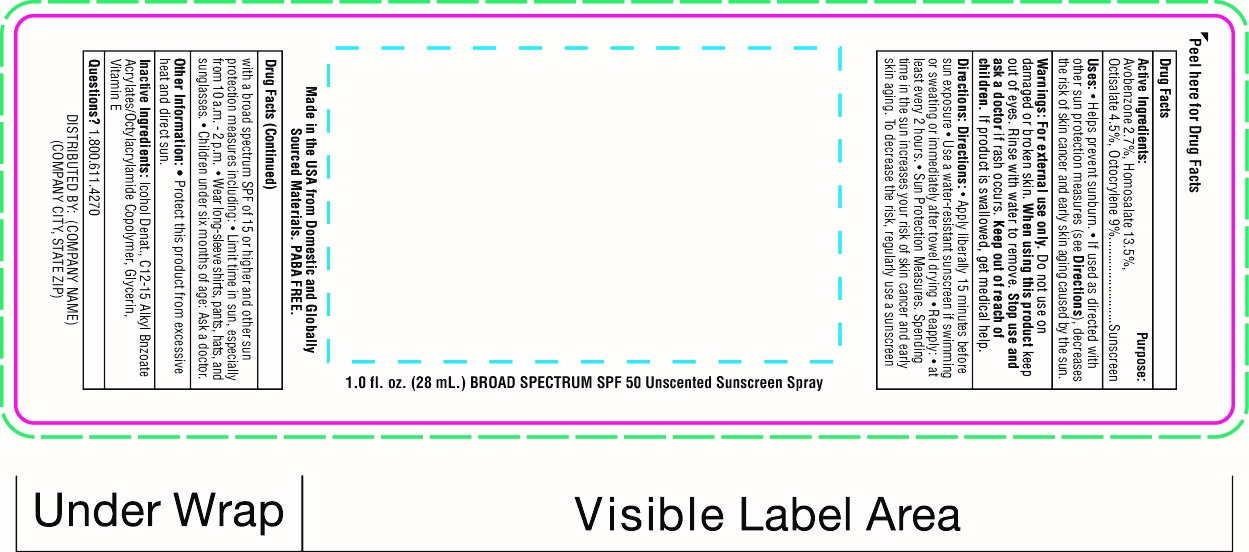 DRUG LABEL: SnugZ SPF 50 Sunscreen Spry
NDC: 76309-525 | Form: SPRAY
Manufacturer: SnugZ USA
Category: otc | Type: HUMAN OTC DRUG LABEL
Date: 20251229

ACTIVE INGREDIENTS: HOMOSALATE 4.2 g/28 mL; OCTISALATE 1.4 g/28 mL; OCTOCRYLENE 2.8 g/28 mL; AVOBENZONE 0.84 g/28 mL
INACTIVE INGREDIENTS: ALCOHOL

ZSUNPL - SPF 50 Sunscreen Spray